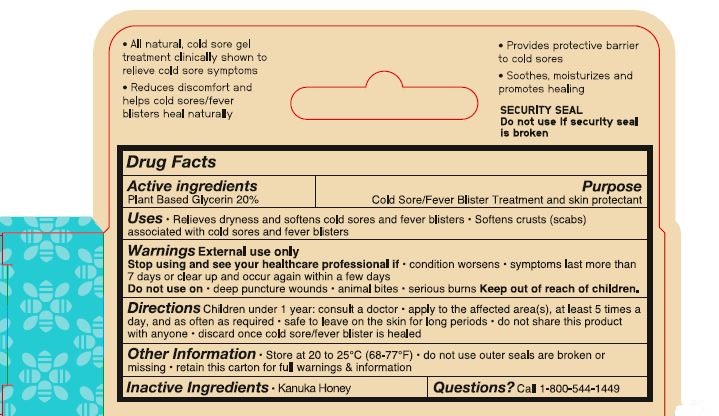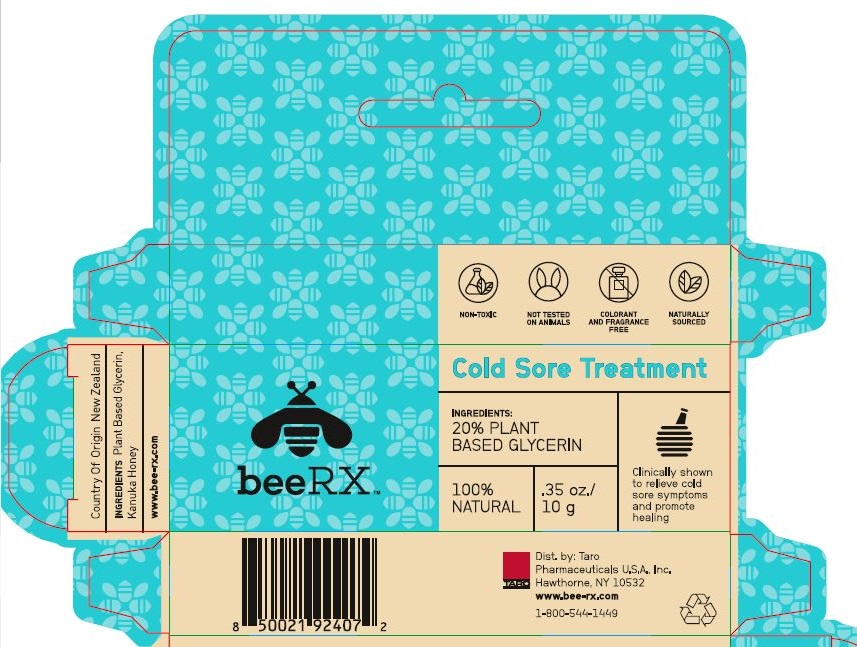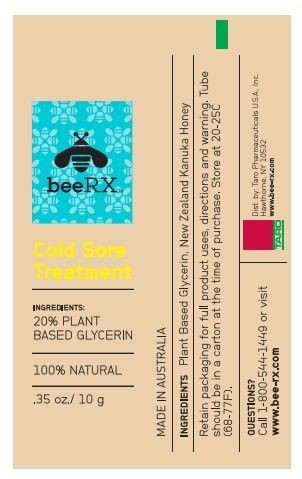 DRUG LABEL: beeRX Cold Sore Treatment
NDC: 51672-5309 | Form: GEL
Manufacturer: Taro Pharmaceuticals U.S.A., Inc.
Category: otc | Type: HUMAN OTC DRUG LABEL
Date: 20250121

ACTIVE INGREDIENTS: GLYCERIN 0.2 g/1 g
INACTIVE INGREDIENTS: HONEY

Drug Facts

Active ingredients | Purpose
Plant based glycerin 20% | Cold Sore/Fever Blister Treatment and skin protectant

Uses

- Relieves dryness and softens cold sores and fever blisters
- Softens crusts (scabs) associated with cold sores and fever blisters

Stop using and see your healthcare professional if

- condition worsens
- symptoms last more than 7 days or clear up and occur again within a few days

Do not use on

- deep puncture wounds
- animal bites
- serious burns

DOSAGE AND ADMINISTRATION

Directions Children under 1 year: consult a doctor

- apply to the affected area(s), at least 5 times a day, and as often as required
- safe to leave on the skin for long periods
- do not share this product with anyone
- discard once cold sore / fever blister is healed

Other Information

- Store at 20 to 25°C (68-77°F)
- do not use outer seals are broken or missing
- retain this carton for full warnings & information

Inactive Ingredients

- Kanuka Honey

TARO
Dist. by: Taro
Pharmaceuticals U.S.A., Inc.
Hawthorne, NY 10532
www.bee-rx.com
1-800-544-1449

PACKAGE LABEL.PRINCIPAL DISPLAY PANEL

beeRX™
NON-TOXIC
NOT TESTED
ON ANIMALS
COLORANT
AND FRAGRANCE
FREE
NATURALLY
SOURCED
Cold Sore Treatment
INGREDIENTS:
20% PLANT
BASED GLYCERIN
100%
NATURAL
.35 oz./
10 g
Clinically shown
to relieve cold
sore symptoms
and promote
healing
Country Of Origin New Zealand
INGREDIENTS Plant Based Glycerin,
Kanuka Honey
www.bee-rx.com
TARO
Dist. by Taro
Pharmaceuticals U.S.A. Inc.
Hawthorne, NY 10532
www.bee-rx.com
1-800-544-1449

- All natural, cold sore gel
  treatment clinically shown to
  relieve cold sore symptoms
- Reduces discomfort and
  help cold sores/fever
  blisters heal naturally
- Provides protective barrier
  to cold sores
- Soothes, moisturizes and
  promotes healing
  SECURITY SEAL
  Do not use if security seal
  is broken

beeRX™
Cold Sore
Treatment
INGREDIENTS:
20% PLANT
BASED GLYCERIN
100% NATURAL
.35 oz. / 10 g
MADE IN AUSTRALIA
INGREDIENTSPlant Based Glycerin, New Zealand Kanuka Honey
Retain packaging for full product uses, directions and warning. Tube
should be in a carton at the time of purchase. Store at 20-25C
(68-77F).
QUESTIONS?
Call 1-800-544-1449 or visit
www.bee-rx.com
TARO
Dist. by: Taro Pharmaceuticals U.S.A., Inc.
Hawthorne, NY 10532
www.bee-rx.com